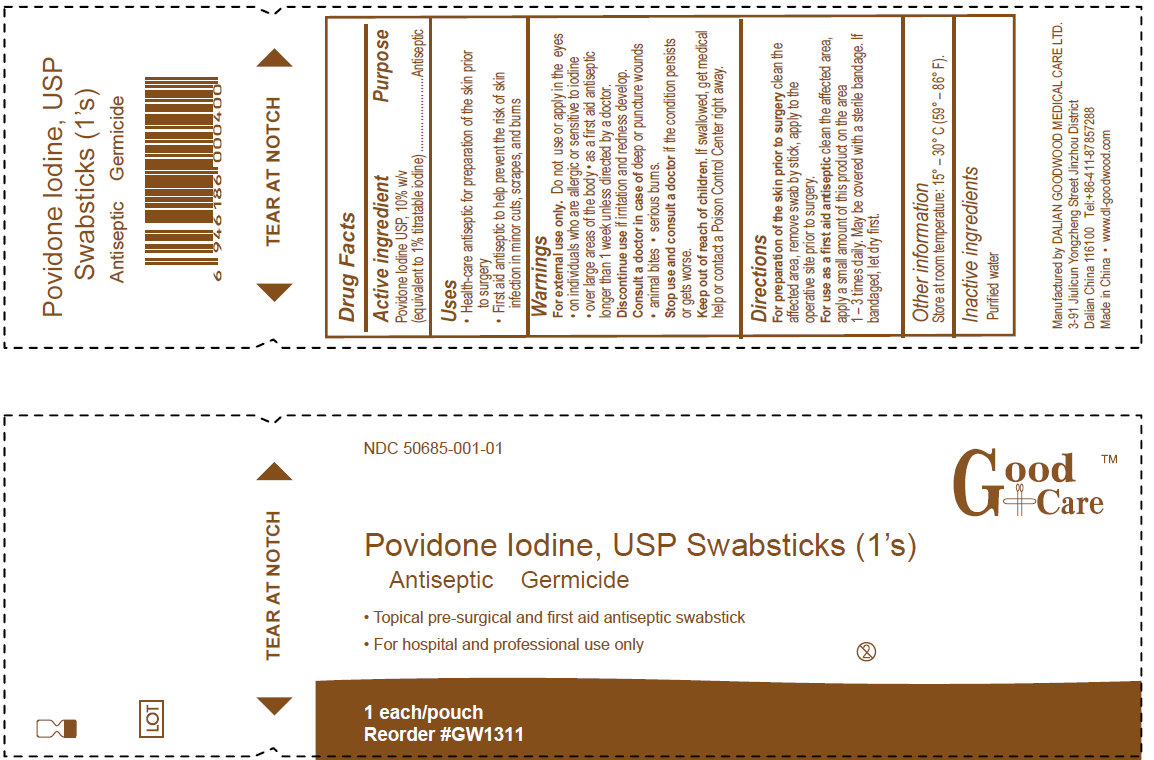 DRUG LABEL: Good Care Povidone Iodine
NDC: 50685-001 | Form: SWAB
Manufacturer: Dalian Goodwood Medical Care Ltd.
Category: otc | Type: HUMAN OTC DRUG LABEL
Date: 20230525

ACTIVE INGREDIENTS: POVIDONE-IODINE 100 mg/1 mL
INACTIVE INGREDIENTS: CITRIC ACID MONOHYDRATE; GLYCERIN; WATER; SODIUM HYDROXIDE

Povidone Iodine, USP Swabsticks

Active Ingredient

Povidone Iodine USP, 10% w/v

(equivalent to 1% titratable iodine)

Purpose

Antiseptic

Uses

- Health-care antiseptic for preparation of the skin prior to surgery
- First aid antiseptic to help prevent the risk of skin infection in minor cuts, scrapes and burns

Warnings

For external use only.

Do not use or apply in the eyes

- on individuals who are allergic or sensitive to iodine
- over large areas of the body
- as a first aid antiseptic longer than 1 week unless directed by a doctor
- Discontinue use if irritation and redness develop.

Stop use and consult a doctor if the condition persists or gets worse.

Keep out of reach of children. If swallowed, get medical help or contact a Poison Control Center right away.

Directions

For preparation of the skin prior to surgery clean the affected area, remove swab by the stick, apply to the operative site prior to surgery.

For use as a first aid antiseptic clean the affected area, apply a small amount of this product on the area 1-3 times daily. May be covered with a sterile bandage. If bandaged, let dry first.

Other information

Store at room temperature: 15 degrees - 30 degrees C (59 degrees - 86 degrees F)

Inactive ingredients

citric acid, glycerin, nonoxynol-8, purified water, sodium hydroxide

Manufactured by DALIAN GOODWOOD MEDICAL CARE LTD.

3-91 Jiulicun Yongzheng Street Jinzhou District Dalian China 116100

Tel: +86-411-87857288

Made in China www.dl-goodwood.com

PACKAGE LABEL

Good Care
Povidone Iodine, USP Swabsticks
Antiseptic Germicide

- Topical pre-surgical and first aid antiseptic swabstick
- For hospital and professional use only